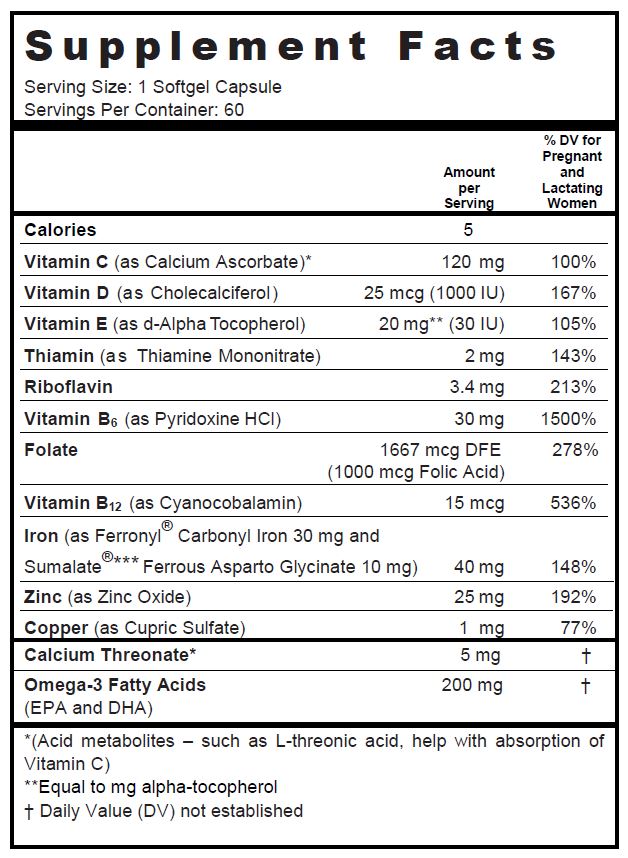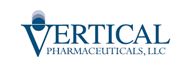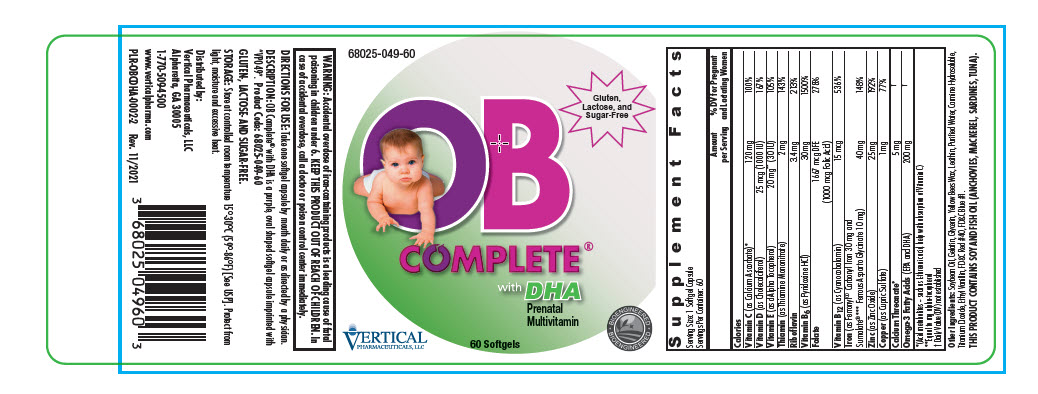 DRUG LABEL: OB Complete DHA
NDC: 68025-049 | Form: CAPSULE, LIQUID FILLED
Manufacturer: Vertical Pharmaceuticals, LLC
Category: other | Type: DIETARY SUPPLEMENT
Date: 20220107

ACTIVE INGREDIENTS: Omega-3 Fatty Acids 200 mg/1 1; Calcium Ascorbate 120 mg/1 1; Calcium Threonate 5 mg/1 1; Cholecalciferol 1000 [iU]/1 1; .Alpha.-Tocopherol, D- 30 [iU]/1 1; Thiamine Mononitrate 2 mg/1 1; Riboflavin 3.4 mg/1 1; Pyridoxine Hydrochloride 30 mg/1 1; Folic Acid 1 mg/1 1; Cyanocobalamin 15 ug/1 1; IRON PENTACARBONYL 30 mg/1 1; Ferrous Asparto Glycinate 10 mg/1 1; Zinc Oxide 25 mg/1 1; Cupric Sulfate 1 mg/1 1
INACTIVE INGREDIENTS: Soybean Oil; Gelatin; Glycerin; Yellow Wax; Water; Lecithin, Soybean; Pigment Red 48; Titanium Dioxide; Ethyl Vanillin; FD&C Red No. 40; FD&C Blue No. 1

OB COMPLETE™ with DHA
Prenatal Multivitamin/Multimineral

SUPPLEMENT FACTS

Other Ingredients: Soybean Oil, Gelatin, Glycerin, Yellow Beeswax, Lecithin, Purified Water, Carmine Hydrosoluble, Titanium Dioxide, Ethyl Vanillin, FD&C Red #40, FD&C Blue #1

THIS PRODUCT CONTAINS SOY AND FISH OIL (ANCHOVIES, MACKEREL, SARDINES, TUNA).

GLUTEN-, LACTOSE- AND SUGAR-FREE

OB Complete® with DHA is a prescription multivitamin/multimineral indicated for use in improving the nutritional status of women prior to conception, throughout pregnancy, and in the postnatal period for both lactating and non-lactating mothers.

CONTRAINDICATIONS

OB Complete™ with DHA should not be used by patients with a known hypersensitivity to any of the listed ingredients including soy and fish oil.

WARNING: Accidental overdose of iron-containing products is a leading cause of fatal poisoning in children under 6. KEEP THIS PRODUCT OUT OF REACH OF CHILDREN. In case of accidental overdose, call a doctor or poison control center immediately.

PRECAUTIONS

Folic acid alone is improper therapy in the treatment of pernicious anemia and other megaloblastic anemias where vitamin B12 is deficient. Folic acid in doses above 0.1 mg daily may obscure pernicious anemia in that hematologic remission can occur while neurologic manifestations remain progressive. Allergic sensitization has been reported following both oral and parenteral administration of folic acid.

The patient’s medical conditions and consumption of other drugs, herbs, and/or supplements should be considered.

DRUG INTERACTIONS

OB Complete® with DHA Prenatal Multivitamin/Multimineral is not recommended for and should not be given to patients receiving levodopa because the action of levodopa is antagonized by pyridoxine. There is a possibility of increased bleeding due to pyridoxine interaction with anticoagulants (e.g., Aspirin, Heparin, Clopidogrel).

ADVERSE REACTIONS

Adverse reactions have been reported with specific vitamins and minerals but generally at levels substantially higher than those contained herein. However, allergic and idiosyncratic reactions are possible at lower levels. Iron, even at the usual recommended levels, has been associated with gastrointestinal intolerance in some patients.

DESCRIPTION

OB Complete® with DHA is a purple, oval shaped softgel capsule imprinted with “VP049”.

DIRECTIONS FOR USE

Take one softgel capsule by mouth daily or as directed by a physician.

HOW SUPPLIED

OB Complete® with DHA Prenatal Multivitamin/Multimineral softgels are available in 60 count bottles.

Product Code: 68025-049-60

STORAGE

Store at controlled room temperature 15°-30°C (59°-86°F) [See USP]. Protect from light, moisture and excessive heat.

HEALTH CLAIM

KEEP THIS PRODUCT OUT OF REACH OF CHILDREN.

***Sumalate® (Ferrous Asparto Glycinate) is a registered trademark of Albion International, Inc. and is covered by the following patents: U.S. Pat. No. 6,716,814; U.S. Pat. No. 8,007,846 and U.S. Pat. No. 8,425,956.

For use on the order of a healthcare practitioner.

Call your doctor about side effects. To report side effects, call Vertical Pharmaceuticals at 1-770-509-4500 or FDA at 1-800-FDA-1088 or www.fda.gov/medwatch.

PLR-OBCDHA-00003-3 Rev. 11/2021

Distributed by:
Vertical Pharmaceuticals, LLC
Alpharetta, GA 30005

1-770-509-4500

www.verticalpharma.com

PRINCIPAL DISPLAY PANEL - 60 Softgel Bottle Label

OB
Complete®
with DHA
Prenatal
Multivitamin

68025-049-60
60 Softgels